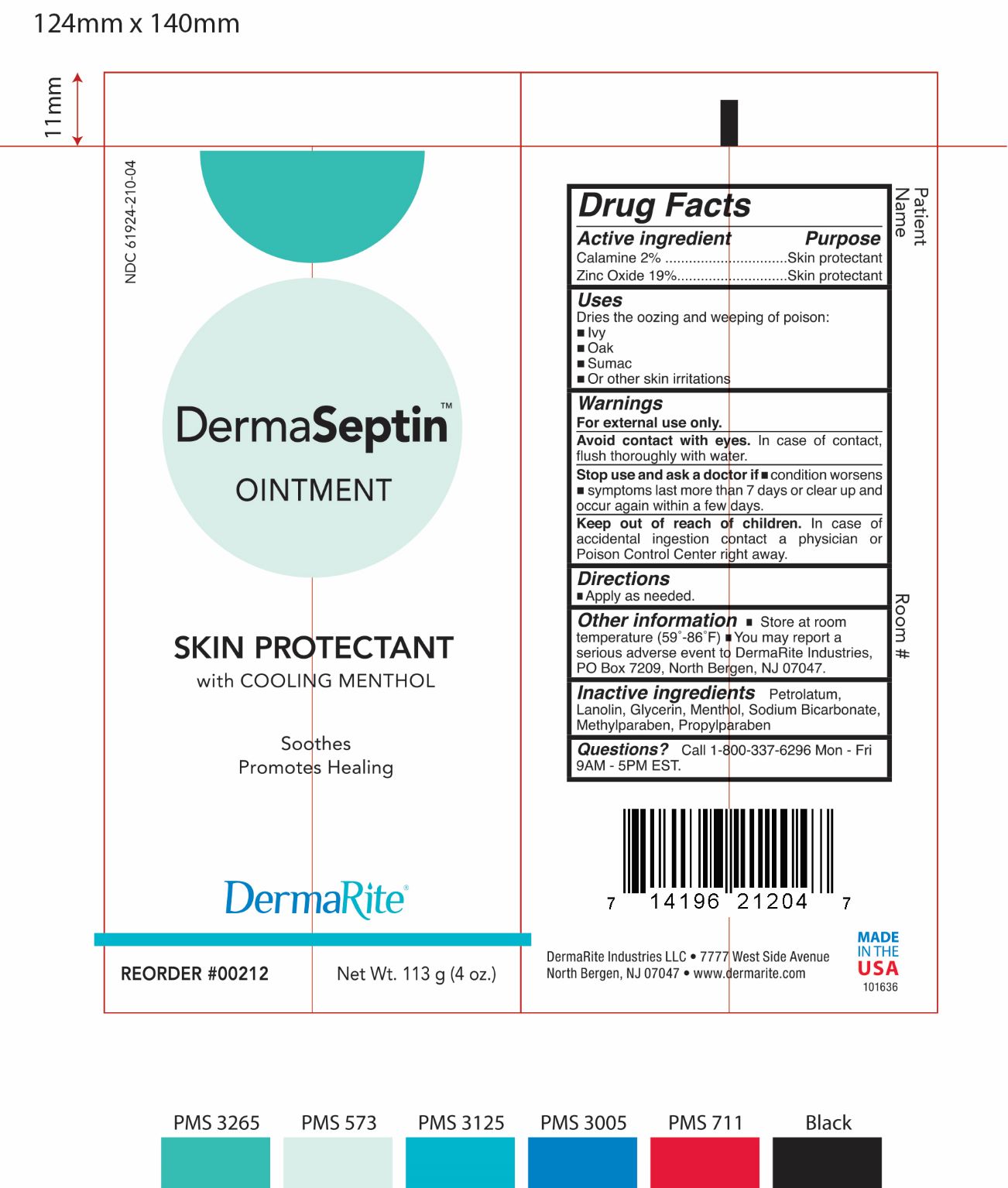 DRUG LABEL: DERMASEPTIN
NDC: 61924-210 | Form: OINTMENT
Manufacturer: DermaRite Industries, LLC
Category: otc | Type: HUMAN OTC DRUG LABEL
Date: 20180913

ACTIVE INGREDIENTS: FERRIC OXIDE RED 2.3 g/1 g; ZINC OXIDE 21.47 g/1 g
INACTIVE INGREDIENTS: GLYCERIN; LANOLIN; METHYLPARABEN; PROPYLPARABEN; SODIUM BICARBONATE; PETROLATUM; MENTHOL

DRUG LISTING: DERMASEPTIN

Active Ingredients

- Zinc Oxide 19%
- Calamine 2%

Purpose:

- Zinc Oxide: Skin protectant
- Calamine : Skin protectant

Uses:

Dries the oozing and weeping of poison:

- Ivy
- Oak
- Sumac
- Or othe skin irritations

Warnings

- For external use only.
- Avoid contact with eyes. In case of contact, flush thoroughly with water.
- Stop use and ask a doctor if condition worsens
- Symptoms last more than 7 days or clear up and occur again within a few days.

Warnings:

- Keep out of reach of children. In case accidental ingestion contact a physician or Poison Control Center right away.

Directions

Applied as needed.

Other Information:

Store at room temperature (59°-86°F).

You may report a serious adverse event to DermaRite Industires, PO Box 7209, North Bergen, NJ 07047.

Inactive Ingredients:

Petrolatum, Lanolin, Glycerin, Menthol, Sodium Bicarbonate, methylparaben, Propylparaben

Questions

Call 1-800-337-6296 Mon-Fri 9AM-5PM EST.